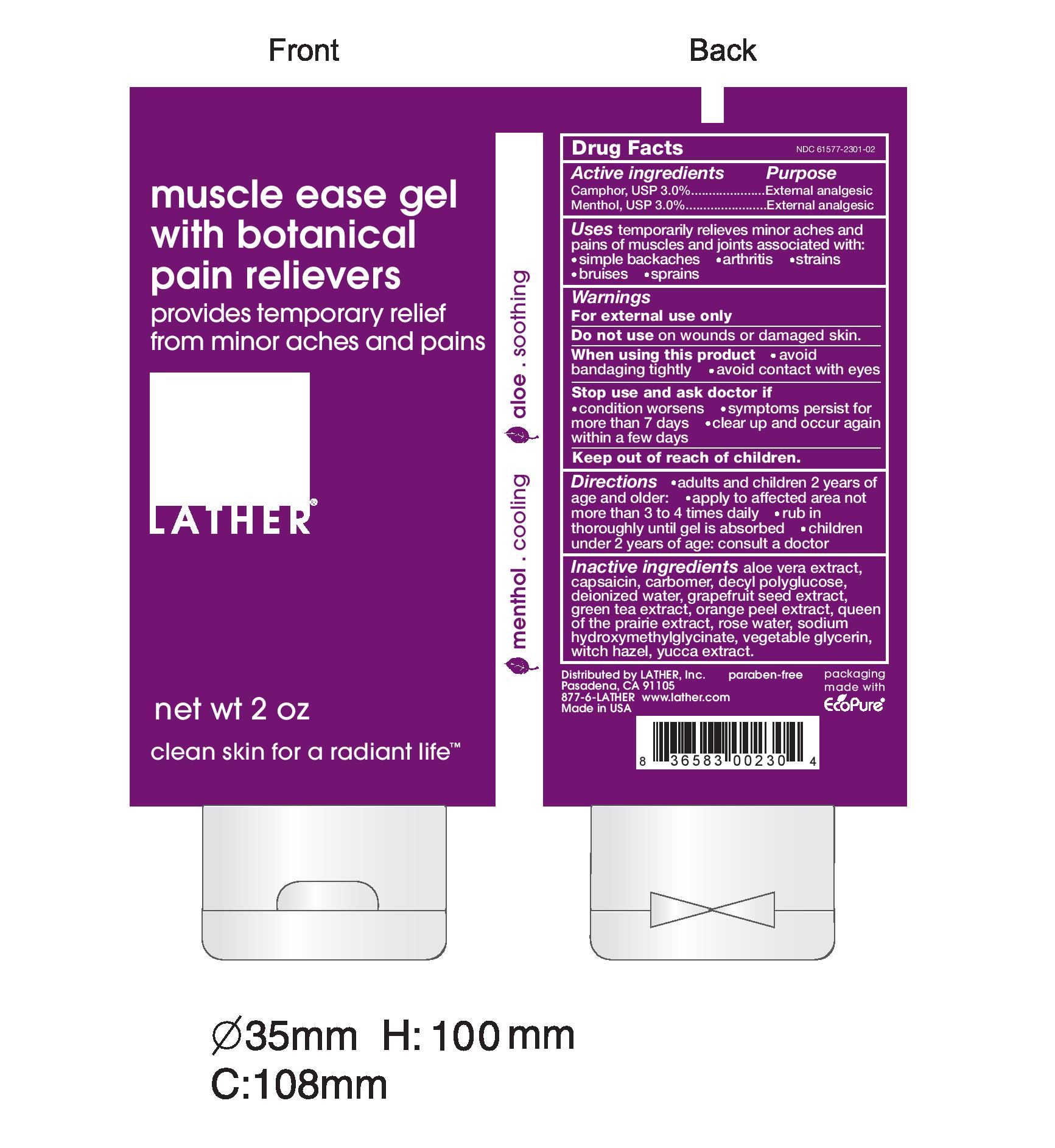 DRUG LABEL: MUSCLE EASE
NDC: 61577-2301 | Form: GEL
Manufacturer: SOMBRA COSMETICS INC.
Category: otc | Type: HUMAN OTC DRUG LABEL
Date: 20250529

ACTIVE INGREDIENTS: MENTHOL 0.03 g/1 g; CAMPHOR (SYNTHETIC) 0.03 g/1 g
INACTIVE INGREDIENTS: ALOE VERA LEAF; CAPSICUM; CARBOMER HOMOPOLYMER TYPE C; DECYL GLUCOSIDE; WATER; GRAPEFRUIT SEED OIL; GREEN TEA LEAF; ORANGE PEEL; FILIPENDULA ULMARIA FLOWER; ROSA CENTIFOLIA FLOWER OIL; SODIUM HYDROXYMETHYLGLYCINATE; GLYCERIN; WITCH HAZEL; YUCCA SCHIDIGERA ROOT

Muscle Ease

Active Ingredients

Menthol USP 3%

Camphor USP 3%

Purpose

EXTERNAL ANALGESIC

Keep out of reach of children

Uses

Temporarily relieves minor aches and pains of muscles and joints associated with: simple backaches, arthritis, strains, bruises, and sprains

Warnings

For external use only. Do not use on wounds or damaged skin. When using this product: avoid bandaging tightly, avoid contact with eyes, keep out of reach of children.

Stop use and ask doctor if: condition worsens, symptoms persist for more than 7 days, clear up and occur again within a few days.

Directions

adults and children 2 years of age and older: apply to affected area not more than 3 to 4 times daily, rub in thoroughly until gel is absorbed, children under 2 years of age: consult a doctor.

Inactive Ingredients

aloe vera extract, capsaicin, carbomer, decyl polyglucose, water, grapefruit seed extract, green tea extract, orange peel extract, queen of the prairie extract, rose water, sodium hydroxymethylglycinate, vegetable glycerin, witch hazel, yucca extract

Questions or Comments

1-800-225-3963